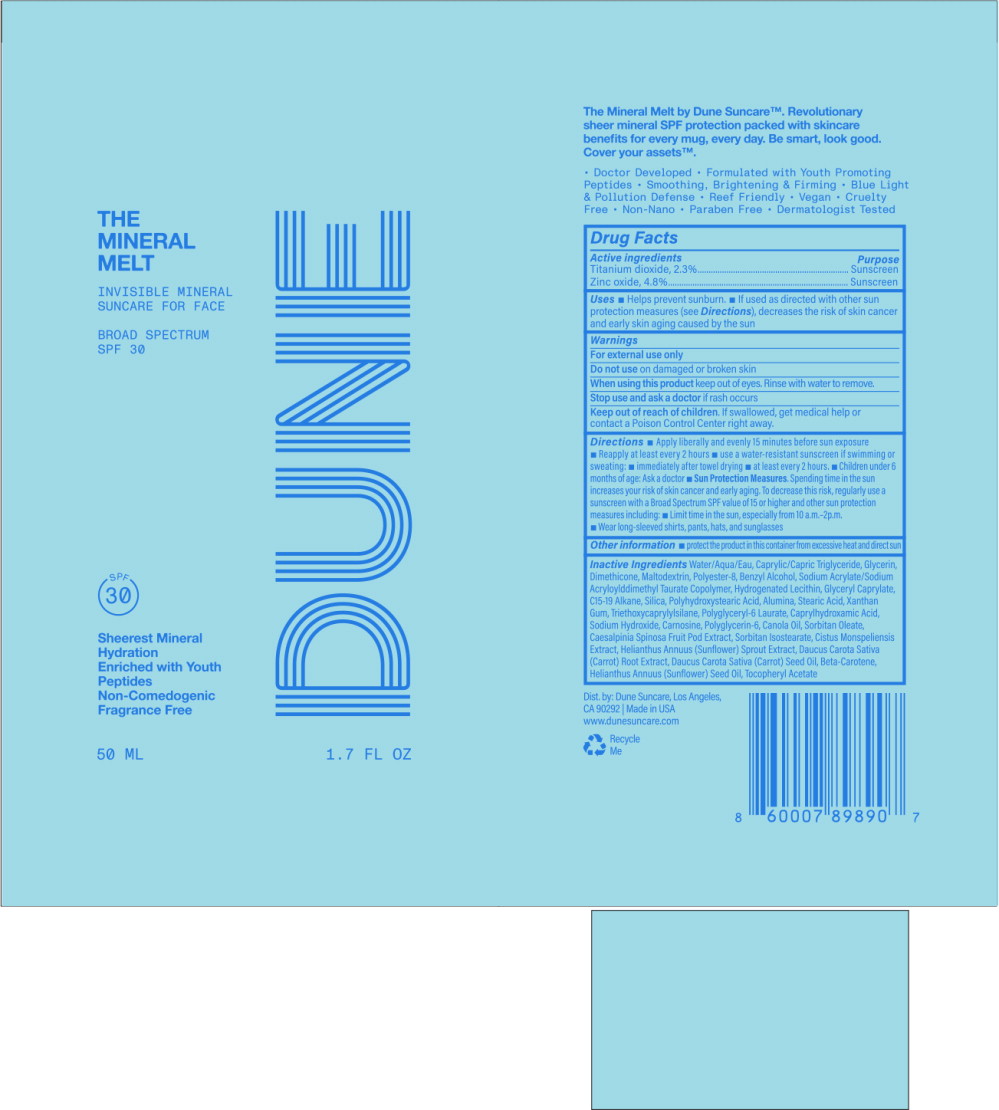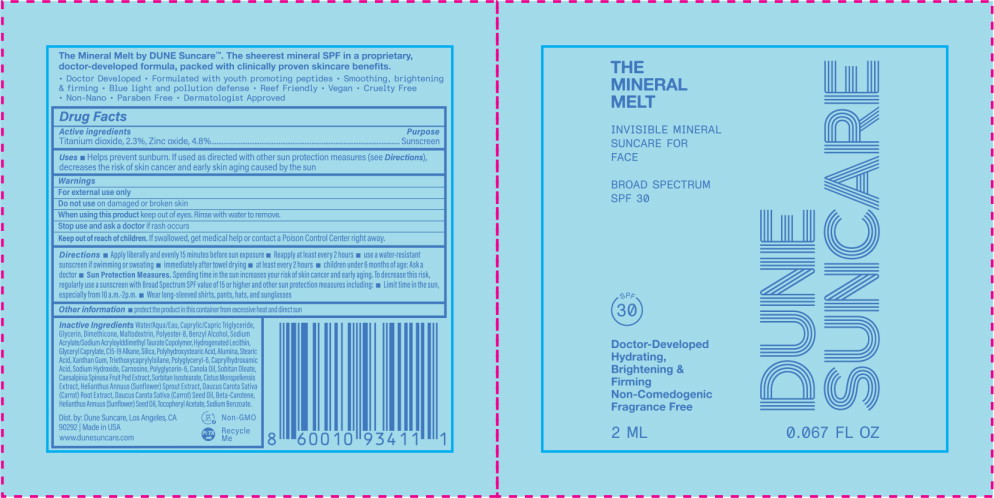 DRUG LABEL: The Mineral Melt SPF30
NDC: 82757-102 | Form: LOTION
Manufacturer: Dune Suncare Inc.
Category: otc | Type: HUMAN OTC DRUG LABEL
Date: 20230601

ACTIVE INGREDIENTS: Zinc Oxide 48 mg/1 mL; Titanium Dioxide 23 mg/1 mL
INACTIVE INGREDIENTS: Water; Medium-Chain Triglycerides; Glycerin; Dimethicone; Maltodextrin; Polyester-8 (1400 MW, CYANODIPHENYLPROPENOYL CAPPED); Benzyl Alcohol; Sodium Acrylate/Sodium Acryloyldimethyltaurate Copolymer (4000000 MW); Hydrogenated Soybean Lecithin; Glyceryl Monocaprylate; C15-19 Alkane; Silicon Dioxide; Polyhydroxystearic Acid (2300 MW); Aluminum Oxide; Stearic Acid; Xanthan Gum; Triethoxycaprylylsilane; Polyglyceryl-6 Laurate; Caprylhydroxamic Acid; Sodium Hydroxide; Caesalpinia Spinosa Fruit Pod; Carnosine; Polyglycerin-6; Canola Oil; Sorbitan Monooleate; Sorbitan Isostearate; Helianthus Annuus Sprout; Cistus Monspeliensis Whole; Carrot; Carrot Seed Oil; Beta Carotene; Sunflower Oil; .Alpha.-Tocopherol Acetate

Drug Facts

Active ingredients

Titanium dioxide, 2.3%

Zinc oxide, 4.8%

Purpose

Sunscreen

Sunscreen

Uses

- Helps prevent sunburn.
- If used as directed with other sun protection measures (see Directions), decreases the risk of skin cancer and early skin aging caused by the sun

Warnings

For external use only

Do not use on damaged or broken skin

When using this product keep out of eyes. Rinse with water to remove.

Stop use and ask a doctor if rash occurs

Keep out of reach of children. If swallowed, get medical help or contact a Poison Control Center right away.

Directions

- Apply liberally and evenly 15 minutes before sun exposure
- Reapply at least every 2 hours
- use a water-resistant sunscreen if swimming or sweating:
  - immediately after towel drying
  - at least every 2 hours.
- Children under 6 months of age: Ask a doctor
- Sun Protection Measures. Spending time in the sun increases your risk of skin cancer and early aging. To decrease this risk, regularly use a sunscreen with a Broad Spectrum SPF value of 15 or higher and other sun protection measures including:
  - Limit time in the sun, especially from 10 a.m.-2p.m.
  - Wear long-sleeved shirts, pants, hats, and sunglasses

Other information

- protect the product in this container from excessive heat and direct sun

Inactive Ingredients

Water/Aqua/Eau, Caprylic/Capric Triglyceride, Glycerin, Dimethicone, Maltodextrin, Polyester-8, Benzyl Alcohol, Sodium Acrylate/Sodium Acryloylddimethyl Taurate Copolymer, Hydrogenated Lecithin, Glyceryl Caprylate, C15-19 Alkane, Silica, Polyhydroxystearic Acid, Alumina, Stearic Acid, Xanthan Gum, Triethoxycaprylylsilane, Polyglyceryl-6 Laurate, Caprylhydroxamic Acid, Sodium Hydroxide, Carnosine, Polyglycerin-6, Canola Oil, Sorbitan Oleate, Caesalpinia Spinosa Fruit Pod Extract, Sorbitan Isostearate, Cistus Monspeliensis Extract, Helianthus Annuus (Sunflower) Sprout Extract, Daucus Carota Sativa (Carrot) Root Extract, Daucus Carota Sativa (Carrot) Seed Oil, Beta-Carotene, Helianthus Annuus (Sunflower) Seed Oil, Tocopheryl Acetate

Principal Display Panel – 50 mL Bottle Label

DUNE

THE
MINERAL
MELT

INVISIBLE MINERAL
SUNCARE FOR FACE

BROAD SPECTRUM
SPF 30

Sheerest Mineral
Hydration
Enriched with Youth
Peptides
Non-Comedogenic
Fragrance Free

50 mL

1.7 FL OZ

Principal Display Panel – 2 mL Packet Label

DUNE
SUNCARE

THE
MINERAL
MELT

INVISIBLE MINERAL
SUNCARE FOR
FACE

BROAD SPECTRUM
SPF 30

Doctor-Developed
Hydrating,
Brightening &
Firming
Non-Comedogenic
Fragrance Free

2 mL

0.067 FL OZ